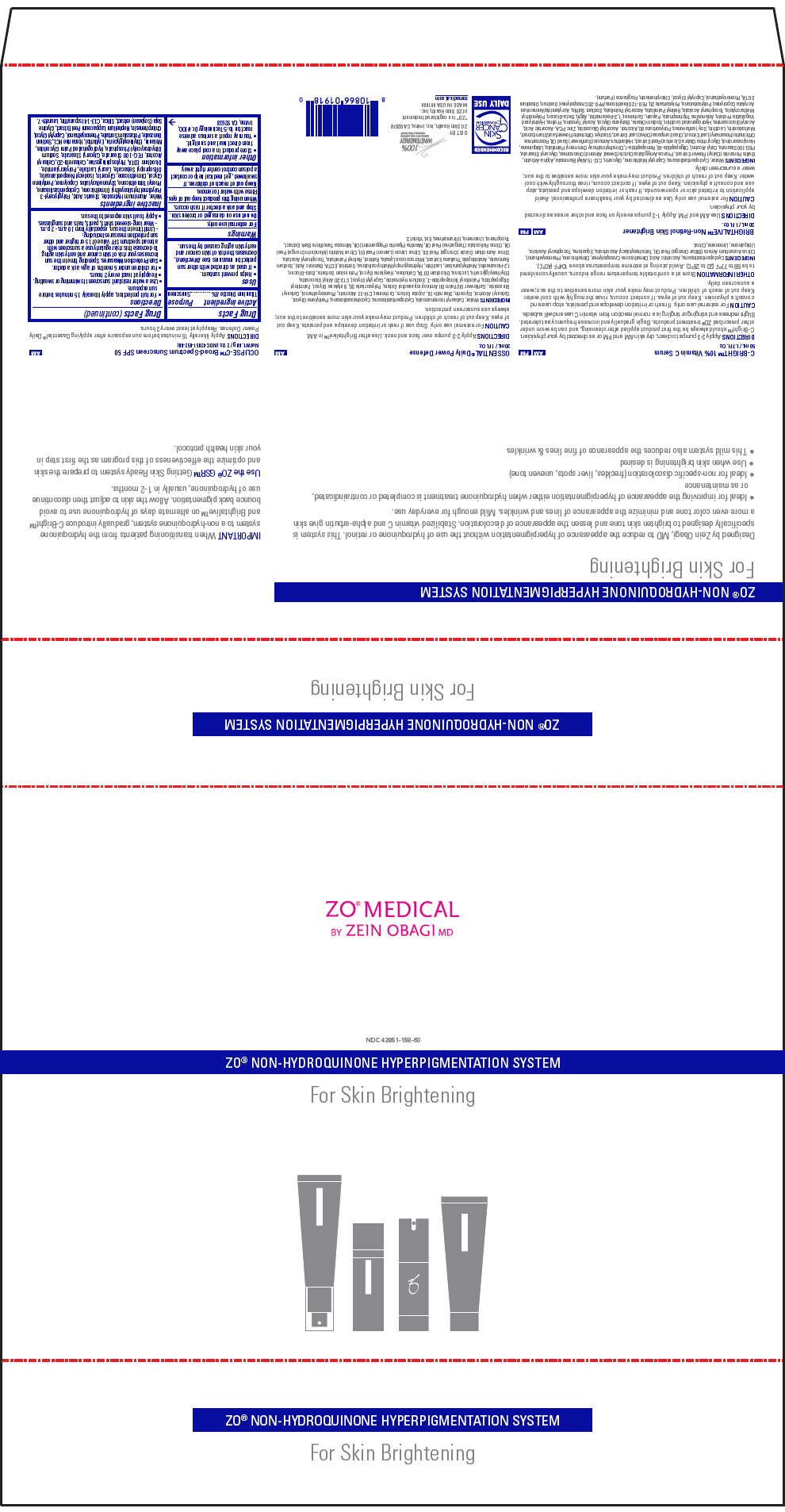 DRUG LABEL: ZO MEDICAL ZO NON-HYDROQUINONE HYPERPIGMENTATION SYSTEM For Skin Brightening
NDC: 42851-158 | Form: KIT | Route: TOPICAL
Manufacturer: ZO Skin Health, Inc.
Category: otc | Type: HUMAN OTC DRUG LABEL
Date: 20160712

ACTIVE INGREDIENTS: Titanium Dioxide 0.08 g/1 g
INACTIVE INGREDIENTS: Water; Aluminum Hydroxide; Stearic Acid; Polyglyceryl-3 Polydimethylsiloxyethyl Dimethicone (4000 MPA.S); Cyclomethicone 5; Phenyl Trimethicone; Pentylene Glycol; Dimethicone; Glycerin; Isodecyl Neopentanoate; Diisopropyl Sebacate; Lauryl Lactate; Edetate Disodium; Phytosphingosine; Polyoxyl 20 Cetostearyl Ether; Cetostearyl Alcohol; PEG-100 Stearate; Glyceryl Monostearate; Sodium Dihydroxycetyl Phosphate; Hydrogenated Palm Glycerides; Melanin Synthetic (Tyrosine, Peroxide); Ethylhexylglycerin; Erythritol; Homarine Hydrochloride; Sodium Benzoate; Potassium Sorbate; Phenoxyethanol; Caprylyl Glycol; Chlorphenesin; Nephelium Lappaceum Fruit Rind; Soybean; Silicon Dioxide; C13-14 Isoparaffin; Laureth-7

ZO® MEDICAL ZO® NON-HYDROQUINONE HYPERPIGMENTATION SYSTEM For Skin Brightening

Drug Facts

Active ingredient

Titanium Dioxide 8%

Purpose

Sunscreen

Uses

- Helps prevent sunburn.
- If used as directed with other sun protection measures (see Directions), decreases the risk of skin cancer and early skin aging caused by the sun.

Warnings

For external use only.

Do not use on damaged or broken skin.

Stop and ask a doctor if rash occurs.

When using this product keep out of eyes. Rinse with water to remove.

Keep out of reach of children. If swallowed, get medical help or contact a poison control center right away.

Other information

- Store product in a cool place away from direct heat and sunlight.
- You may report a serious adverse reaction to: 5 Technology Dr. #100, Irvine, CA 92618

Directions

- For full protection, apply liberally 15 minutes before sun exposure.
- Use a water resistant sunscreen if swimming or sweating.
- Reapply at least every 2 hours.
- For children under 6 months of age: ask a doctor.
- Sun Protection Measures. Spending time in the sun increases your risk of skin cancer and early skin aging. To decrease this risk regularly use a sunscreen with a broad spectrum SPF value of 15 or higher and other sun protection measures including:
  - Limit time in the sun, especially from 10 a.m.- 2 p.m.
  - Wear long-sleeved shirts, pants, hats and sunglasses.
- Apply to all skin exposed to the sun.

Inactive ingredients

Water, Aluminum Hydroxide, Stearic Acid, Polyglyceryl-3 Polydimethylsiloxyethyl Dimethicone, Cyclopentasiloxane, Phenyl Trimethicone, Styrene/Acrylates Copolymer, Pentylene Glycol, Dimethicone, Glycerin, Isodecyl Neopentanoate, Diisopropyl Sebacate, Lauryl Lactate, Polyacrylamide, Disodium EDTA, Phytosphingosine, Ceteareth-20, Cetearyl Alcohol, PEG-100 Stearate, Glyceryl Stearate, Sodium Dihydroxycetyl Phosphate, Hydrogenated Palm Glycerides, Melanin, Ethylhexylglycerin, Erythritol, Homarine HCL, Sodium Benzoate, Potassium Sorbate, Phenoxyethanol, Caprylyl Glycol, Chlorphenesin, Nephelium Lappaceum Peel Extract, Glycine Soja (Soybean) extract, Silica, C13-14 Isoparaffin, Laureth-7.

DIST BY
ZO Skin Health, Inc. Irvine, CA 92618

PRINCIPAL DISPLAY PANEL - Kit Carton

ZO® MEDICAL
BY ZEIN OBAGI MD

NDC 42851-158-60

ZO® NON-HYDROQUINONE HYPERPIGMENTATION SYSTEM

For Skin Brightening